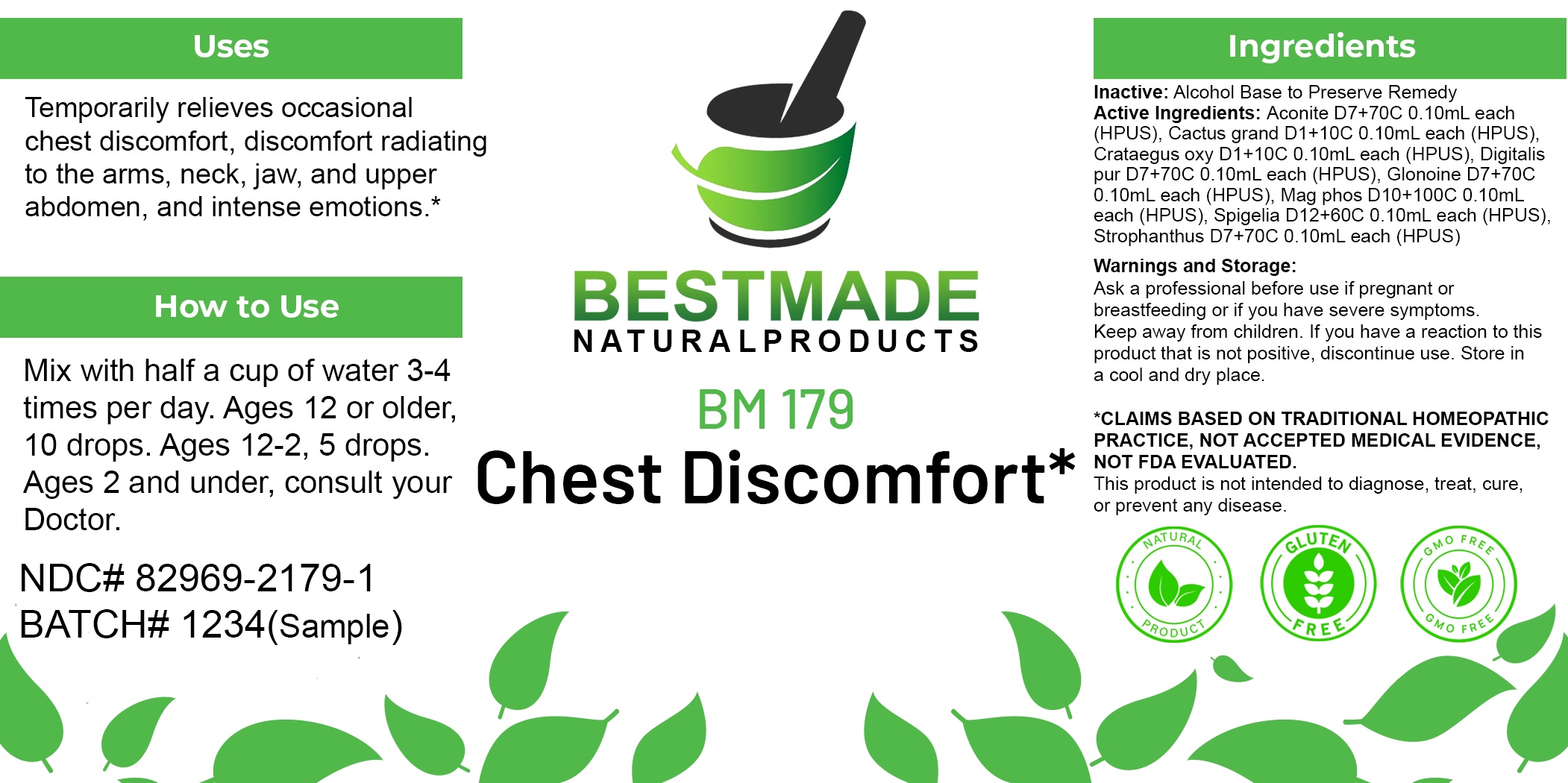 DRUG LABEL: Bestmade Natural Products BM179
NDC: 82969-2179 | Form: LIQUID
Manufacturer: Bestmade Natural Products
Category: homeopathic | Type: HUMAN OTC DRUG LABEL
Date: 20250219

ACTIVE INGREDIENTS: MAGNESIUM PHOSPHATE, DIBASIC TRIHYDRATE 30 [hp_C]/30 [hp_C]; SELENICEREUS GRANDIFLORUS STEM 30 [hp_C]/30 [hp_C]; STROPHANTHUS HISPIDUS SEED 30 [hp_C]/30 [hp_C]; HAWTHORN LEAF WITH FLOWER 30 [hp_C]/30 [hp_C]; ACONITUM NAPELLUS 30 [hp_C]/30 [hp_C]; SPIGELIA ANTHELMIA WHOLE 30 [hp_C]/30 [hp_C]; NITROGLYCERIN 30 [hp_C]/30 [hp_C]; DIGITALIS 30 [hp_C]/30 [hp_C]
INACTIVE INGREDIENTS: ALCOHOL 30 [hp_C]/30 [hp_C]

BM179

DOSAGE AND ADMINISTRATION

How to Use

Mix with half a cup of water 3-4 times per day. Ages 12 or older, 10 drops. Ages 12-2, 5 drops. Ages 2 and under, consult your Doctor.

Inactive:

Alcohol Base to Preserve Product

ACTIVE INGREDIENT

Active Ingredients: Aconite D7+70C 0.10mL each (HPUS), Cactus grand D1+10C 0.10mL each (HPUS), Crataegus oxy D1+10C 0.10mL each (HPUS), Digitalis pur D7+70C 0.10mL each (HPUS), Glonoine D7+70C 0.10mL each (HPUS), Mag phos D10+100C 0.10mL each (HPUS), Spigelia D12+60C 0.10mL each (HPUS), Strophanthus D7+70C 0.10mL each (HPUS)

Uses
Temporarily relieves occasional chest discomfort, discomfort radiating to the arms, neck, jaw, and upper abdomen, and intense emotions.*

Uses
Temporarily relieves occasional chest discomfort, discomfort radiating to the arms, neck, jaw, and upper abdomen, and intense emotions.*

KEEP OUT OF REACH OF CHILDREN

Warnings and Storage:

Ask a professional before use if pregnant or breastfeeding or if you have severe symptoms.

Keep away from children. If you have a reaction to this product that is not positive, discontinue use. Store in a cool and dry place

*CLAIMS BASED ON TRADITIONAL HOMEOPATHIC PRACTICE, NOT ACCEPTED MEDICAL EVIDENCE NOT FDA EVALUATED.
This product is not intended to diagnose, treat, cure, or prevent any disease.

Warnings and Storage:

Ask a professional before use if pregnant or breastfeeding or if you have severe symptoms.

Keep away from children. If you have a reaction to this product that is not positive, discontinue use. Store in a cool and dry place

*CLAIMS BASED ON TRADITIONAL HOMEOPATHIC PRACTICE, NOT ACCEPTED MEDICAL EVIDENCE NOT FDA EVALUATED.
This product is not intended to diagnose, treat, cure, or prevent any disease.

Entire package label